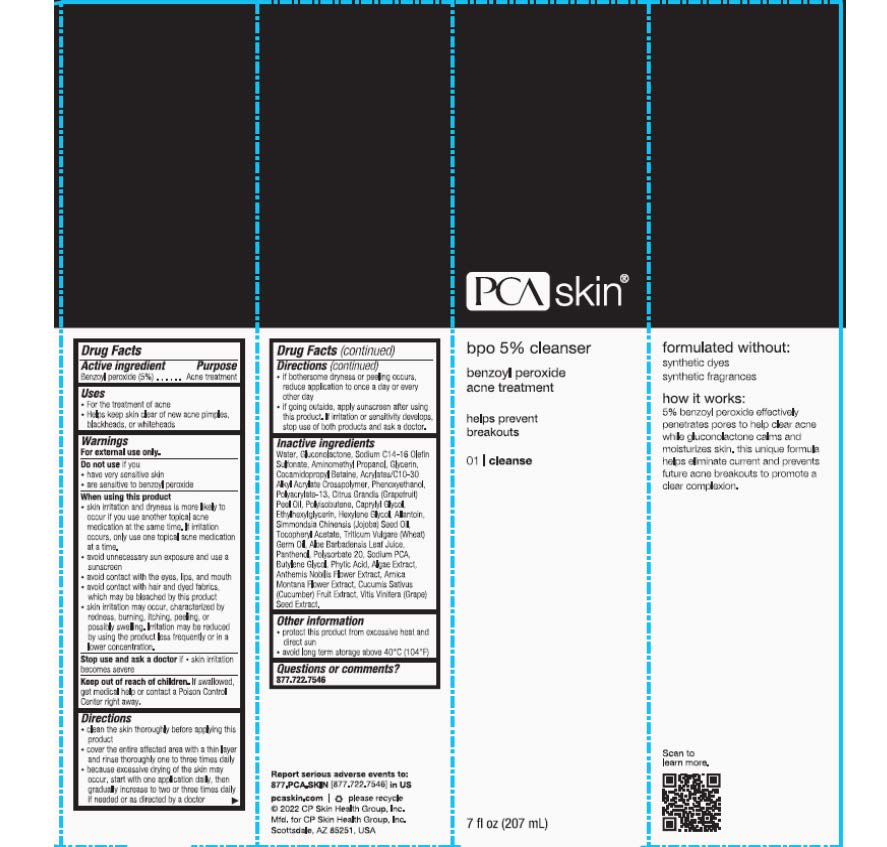 DRUG LABEL: PCA SKIN BPO Cleanser
NDC: 68726-168 | Form: GEL
Manufacturer: CP Skin Health Group, Inc.
Category: otc | Type: HUMAN OTC DRUG LABEL
Date: 20241203

ACTIVE INGREDIENTS: BENZOYL PEROXIDE 5 g/100 mL
INACTIVE INGREDIENTS: ALOE VERA LEAF; WATER; GLYCERIN; .ALPHA.-TOCOPHEROL ACETATE, D-; CAPRYLYL GLYCOL; HEXYLENE GLYCOL; ETHYLHEXYLGLYCERIN; POLYSORBATE 20; BUTYLENE GLYCOL; PHENOXYETHANOL; GLUCONOLACTONE; COCAMIDOPROPYL BETAINE; AMINOMETHYLPROPANOL; ARNICA MONTANA; CHAMAEMELUM NOBILE FLOWER; CUCUMBER; GRAPE; CITRUS PARADISI SEED; WHEAT GERM; ALLANTOIN; PANTHENOL; FYTIC ACID

pHaze 31 BPO Cleanser

Active Ingredient: Benzoyl Peroxide (5.0%)

Purpose: Acne Cleanser

INDICATIONS AND USAGE

Uses: For the treatment of acne. Helps keep skin clear of new acne pimples, blackheads and/or whiteheads.

WARNINGS

Warnings: When using this product,avoid unnecessary sun exposure and use a sunscreen.

____________________________________________________________________________

For external use only.

____________________________________________________________________________

Using other topical acne drugs at the same time or immediately following the sue of this product may increase dryness or irritation of the skin. If this occurs, only one drug should be sued unless directed by a physician.

_________________________________________________________________________________________

Do not use in or near the eyes.

Keep out of reach of children.If swallowed, get medical help or contact Poison Control Center immediately.

Directions:

- Apply a small amount of cleanser to damp skin with fingertips and massage into a light foaming lather.
- Wash in a gentle circular motion.
- Rinse with warm (not hot) water and pat dry.
- Start with one treatment daily or as directed by a physician.

INACTIVE INGREDIENT

Inactive Ingredients: Water/Aqua/Eau, Gluconolactone, Sodium C14-16 Olefin Sulfonate, Aminomethyl Propanol, Glycerin, Cocamidopropyl Betaine, Aloe Babadensis Leaf Juice, Sodium PCA, Tocopheryl Acetate, Allantoin, Panthenol, Phytic Acid, Triticum Vulgare (Wheat) Germ Oil, Simmondsia Chinensis (Jojoba) Seed Oil, Anthemis Nobilis Flower Extract, Vitis Vinifera (Grape) Seed Extract, Cucumis Sativus (Cucumber) Fruit Extract, Arnica Montana Flower Extract, Algae Extract, Acrylates/C10-30 Alkyl Acrylate Crosspolymer, Polyacrylate-13, Caprylyl Glycol, Polisobutene, Ehtylhexylglycerin, Hexylene Glycol, Polysorbate 20, Butylene Glycol, Phenoxyethanol, Citrus Grandis (Grapefruit) Peel Oil.